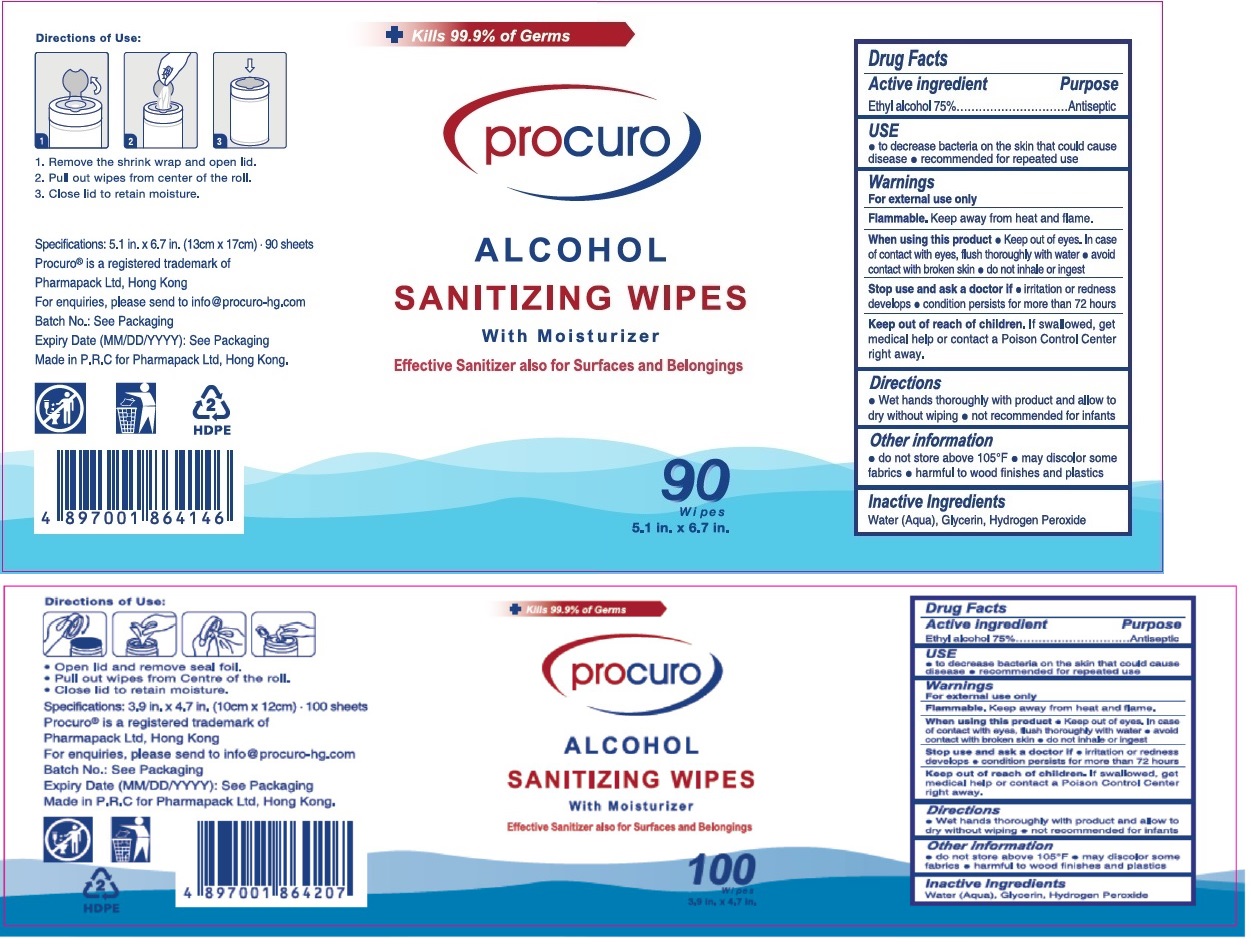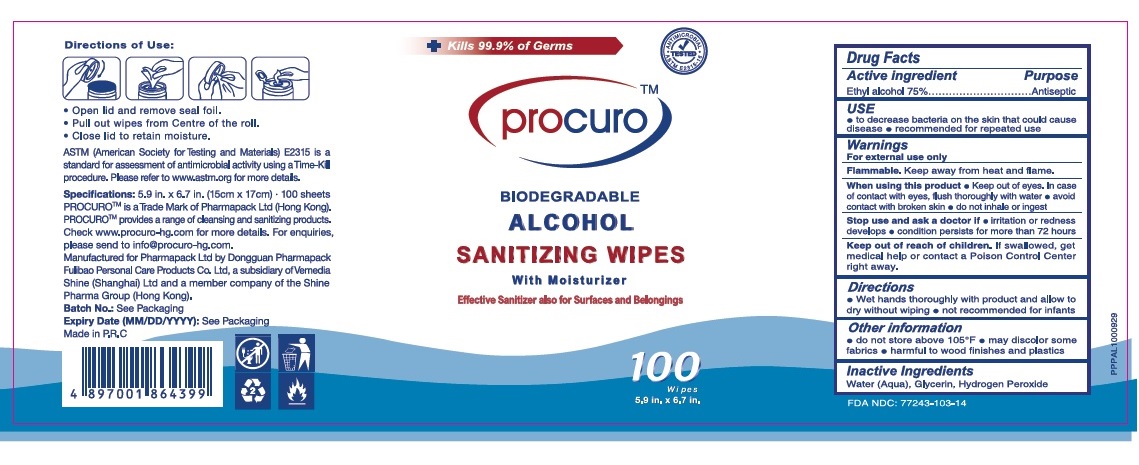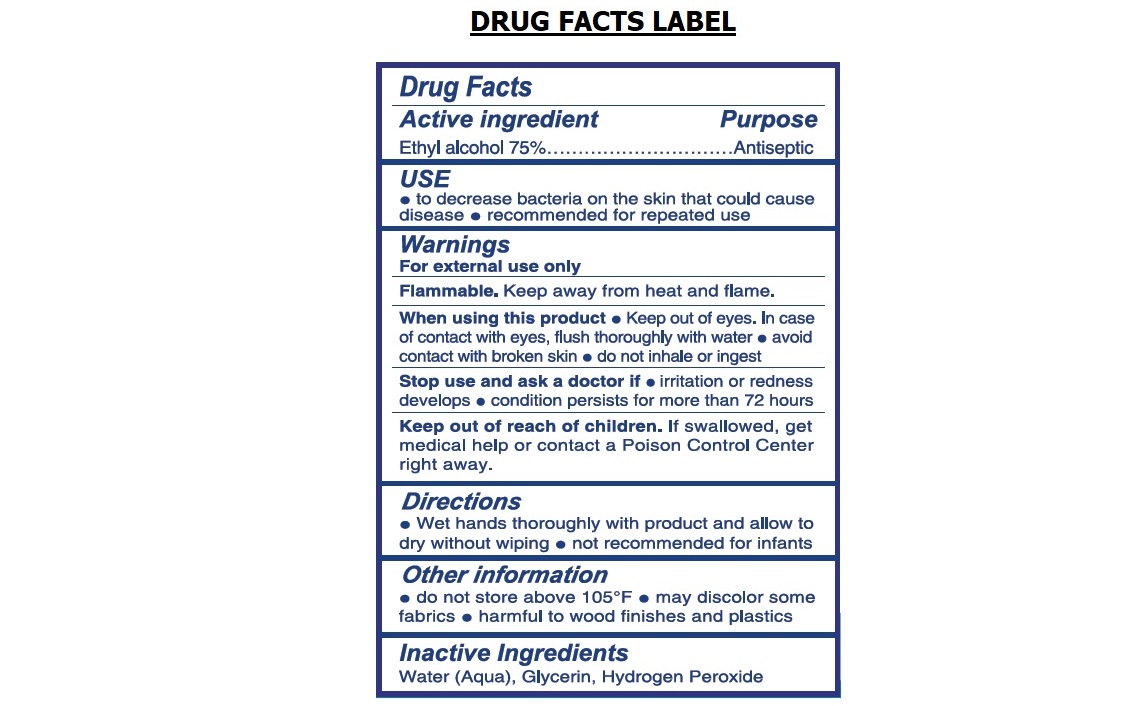 DRUG LABEL: Procuro ALCOHOL SANITIZING WIPES
NDC: 77243-103 | Form: CLOTH
Manufacturer: Dongguan Pharmapack Fulibao Personal Care Products Ltd
Category: otc | Type: HUMAN OTC DRUG LABEL
Date: 20240130

ACTIVE INGREDIENTS: ALCOHOL 75 mL/100 mL
INACTIVE INGREDIENTS: WATER; GLYCERIN; HYDROGEN PEROXIDE

procuro ALCOHOL SANITIZING WIPES

Active ingredient

Ethyl alcohol 75%

Purpose

Antiseptic

USE

• to decrease bacteria on the skin that could cause disease • recommended for repeated use.

Warnings

For external use only.

Flammable.Keep away from heat and flame.

When using this product• Keep out of eyes.In case of contact with eyes，flush thoroughly with water • avoid contact with broken skin • do not inhale or ingest.

Stop use and ask a doctor if• irritation or redness develops • condition persists for more than 72 hours.

Keep out of reach of children.If swallowed, get medical help or contact a Poison Control Center right away.

Directions

• Wet hands thoroughly with product and allow to dry without wiping • not recommended for infants.

Other information

• do not store above 105°F • may discolor some fabrics • harmful to wood finishes and plastics.

Inactive Ingredients

Water(Aqua), Glycerin, Hydrogen Peroxide

Kills 99.9% of Germs

BIODEGRADABLE

ALCOHOL

with Moisturizer

Effective Sanitizer also for Surfaces and Belongings

ANTIMICROBIAL • ASTM E2315-16 • TESTED

Directions of Use:

1.Remove the shrink wrap and open lid.

2.Pull out wipes frim center of the roll.

3.Close lid to retain moisture.

ASTM (American Society for Testing and Materials) E2315 is a standard for assessment of antimicrobial activity using a Time-Kill procedure. Please refer to www.astm.org for more details.

Procuro®is a registered trademark of Pharmapack Ltd, Hong Kong. For enquiries, please send to info@procuro-hg.com

PROCUROTMprovides a range of cleansing and sanitizing products. Check www. procuro-hg.com for more details.

Manufactured for Pharmapack Ltd by Dongguan Pharmapack Fulibao Personal Care Products Co. Ltd, a subsidiary of Vemedia Shine (Shanghai) Ltd and a member company of the Shine Pharma Group (Hong Kong).

Made in P.R.C for Pharmapack Ltd, Hong Kong.